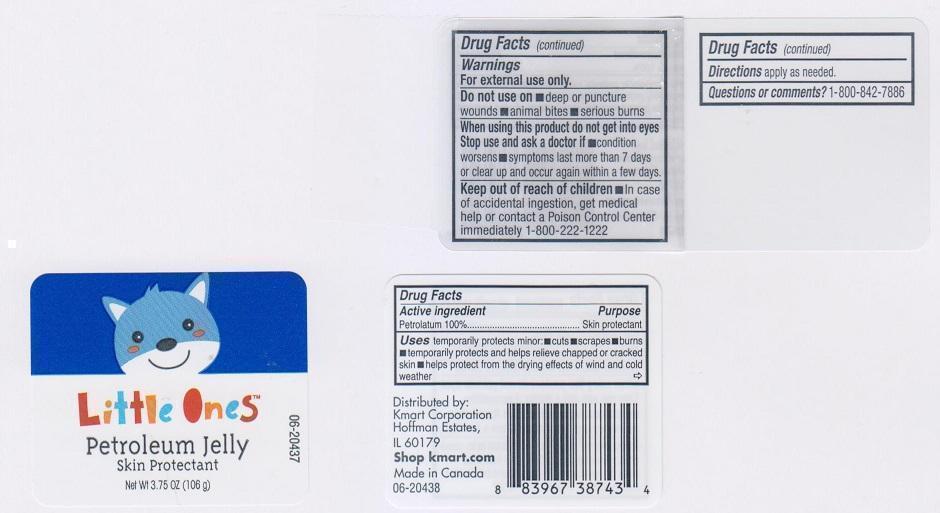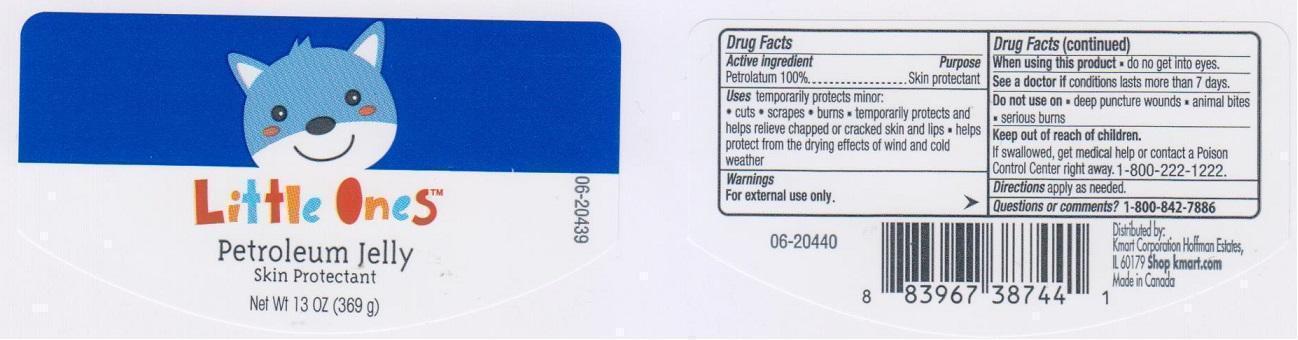 DRUG LABEL: LITTLE ONES PETROLEUM
NDC: 49738-351 | Form: JELLY
Manufacturer: KMART CORPORATION
Category: otc | Type: HUMAN OTC DRUG LABEL
Date: 20150910

ACTIVE INGREDIENTS: PETROLATUM 1000 mg/1 g

DRUG FACTS

Active ingredient

Petrolatum 100%

Purpose

Skin Protectant

Uses

Temporarily protects minor:

- cuts
- scrapes
- burns
- temporarily protects and helps relieve chapped or cracked skin and lips
- helps protect from the drying effects of wind and cold weather

Warnings

For external use only

When using this product

do not get into eyes

Stop use and ask a doctor if

- condition worsens
- symptoms last more than 7 days or clear up and occur again within a few days

Do not use on

- deep or puncture wounds
- animal bites
- serious burns

Keep out of reach of children

In case of accidentl ingestion, get medical help or contact a poison control center immediately 1-800-222-1222

Directions

apply as needed

Questions or comments?

1-800-842-7886